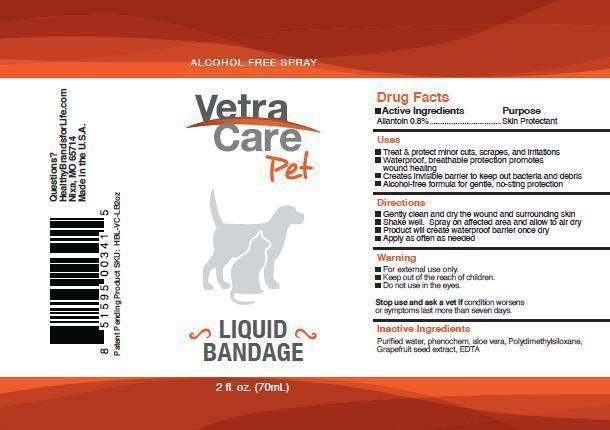 DRUG LABEL: Allantoin .4%
NDC: 51098-501 | Form: LIQUID
Manufacturer: avadim II, LLC
Category: animal | Type: OTC ANIMAL DRUG LABEL
Date: 20131001

ACTIVE INGREDIENTS: Allantoin 4 g/1000 mL
INACTIVE INGREDIENTS: ALOE 1 g/1000 mL; water 950 mL/1000 mL; silicon 3 g/1000 mL

PACKAGE LABEL

Alcohol Free Spray

VetraCare Pet Liquid Bandage

2 fl oz (60ml)

Image

LB2.jpg LB2

Active ingredient Allantoin .8% Skin Protectant

Uses

Treat and protect minor cuts, scrapes, and irritations

waterproof, breathable protection promotes wound healing

Creates invisible barrier to keep out bacteria and debris

Alcohol free formula for gentle, no sting protection

Directions

Gently clean and dry the wound and surrounding skin

shake well. Spray onto affected area and allow to air dry

product will create waterproof barrier once dry

Apply as often as needed

Warning

For external use only

Keep out of the reach of children

Do not use in the eyes

Stop use and ask a vet if condition worsens or symptoms last more than seven days.

Inactive ingredients

Purified water, phenochem, aloe vera, polydimethylsiloxane, grapefruit seed extract, EDTA